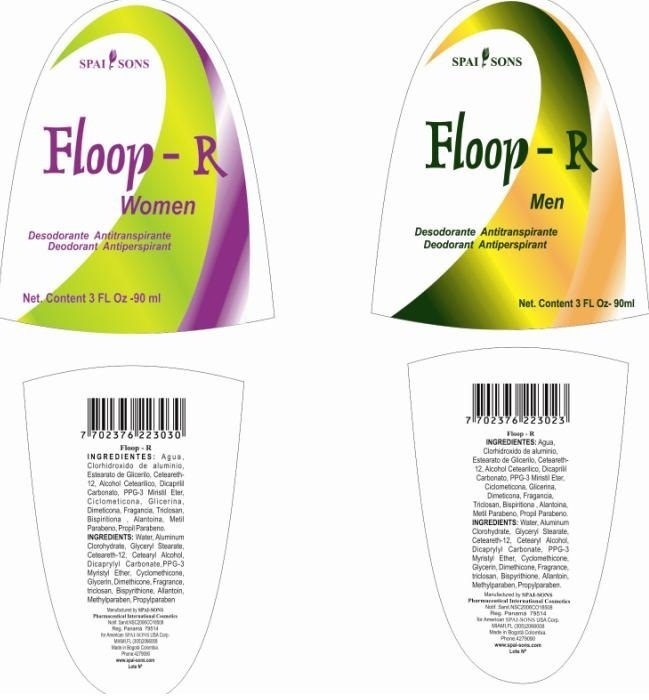 DRUG LABEL: SPAI-SONS
NDC: 66854-008 | Form: EMULSION
Manufacturer: SPAI SONS PHARMACEUTICAL INTERNATIONAL COSMETICS
Category: otc | Type: HUMAN OTC DRUG LABEL
Date: 20120523

ACTIVE INGREDIENTS: ALUMINUM CHLOROHYDRATE 280 mL/1000 mL
INACTIVE INGREDIENTS: WATER; STEARETH-2; CETEARETH-12; STEARYL ALCOHOL; POLYOXYL 20 CETOSTEARYL ETHER; DISTEARYL ETHER; PPG-3 MYRISTYL ETHER; CYCLOMETHICONE; DIMETHICONE; DIISOPROPYL ADIPATE; DICAPRYLYL CARBONATE; GLYCERIN; DIPYRITHIONE; ALLANTOIN; METHYLPARABEN; PROPYLPARABEN; TRICLOSAN

SPAI-SONS FLOOP R

ACTIVE INGREDIENT

This product is owned as a deodorant active ingredients triclosan and aluminum chlorhydroxyde. Mixed effect that produced is deodorant and antiperspirant.

PURPOSE

Floop is an anti-bacterial and antiperspirant high protection modern biotechnical design deodorant.

KEEP OUT OF REACH OF CHILDREN

This product must be keep out reach of children.

INDICATIONS AND USAGE

This product is designed for use in armpit areas as may cause irritation in the area of application by the sensitivity of the user.

WARNINGS

Hypersensivity may result in the area of application, not consume this product, if swallowed consult your doctor.

DOSAGE AND ADMINISTRATION

This product is topical application apply the amount necessary in desirable area and rub gently.

INACTIVE INGREDIENT

The design of this product does humectant agents to give best feeling in the skin effect in addition to produce antiperspirant and deodorant.

IMAGE OF THE LABEL